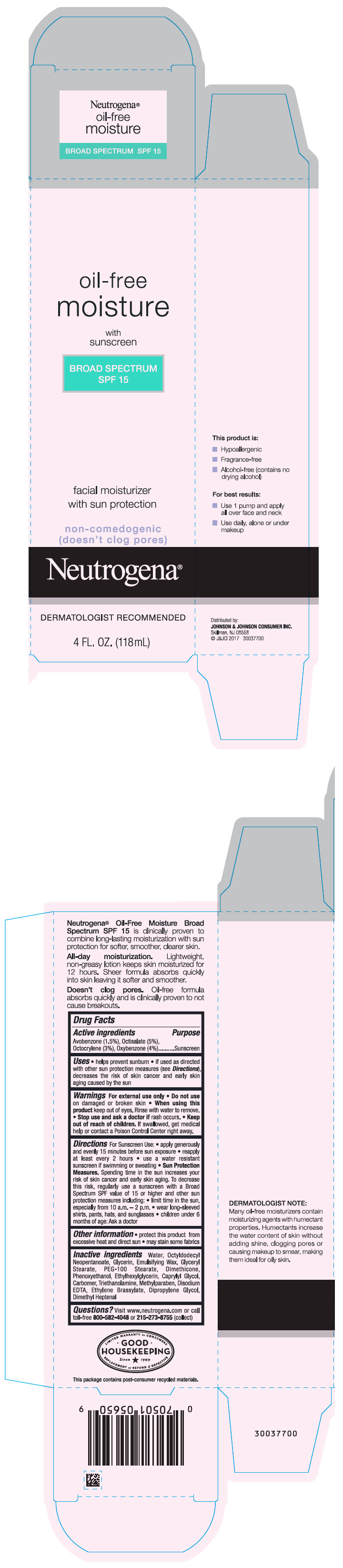 DRUG LABEL: Neutrogena Oil Free Moisture Broad Spectrum SPF15
NDC: 69968-0616 | Form: LOTION
Manufacturer: Kenvue Brands LLC
Category: otc | Type: HUMAN OTC DRUG LABEL
Date: 20251106

ACTIVE INGREDIENTS: OXYBENZONE 40 mg/1 mL; AVOBENZONE 15 mg/1 mL; OCTISALATE 50 mg/1 mL; OCTOCRYLENE 30 mg/1 mL
INACTIVE INGREDIENTS: WATER; OCTYLDODECYL NEOPENTANOATE; GLYCERIN; GLYCERYL MONOSTEARATE; PEG-100 STEARATE; DIMETHICONE; PHENOXYETHANOL; ETHYLHEXYLGLYCERIN; CAPRYLYL GLYCOL; CARBOXYPOLYMETHYLENE; TROLAMINE; METHYLPARABEN; EDETATE DISODIUM ANHYDROUS; ETHYLENE BRASSYLATE; DIPROPYLENE GLYCOL; 2,6-DIMETHYL-5-HEPTENAL

Neutrogena® oil-free moisture with sunscreen BROAD SPECTRUM SPF 15

Drug Facts

ACTIVE INGREDIENT

Active ingredients | Purpose
Avobenzone 1.5% | Sunscreen
Octisalate 5% | Sunscreen
Octocrylene 3% | Sunscreen
Oxybenzone 4% | Sunscreen

Uses

- helps prevent sunburn
- if used as directed with other sun protection measures (see Directions), decreases the risk of skin cancer and early skin aging caused by the sun

Warnings

For external use only

- Do not use on damaged or broken skin

- When using this product keep out of eyes. Rinse with water to remove.

- Stop use and ask a doctor if rash occurs

- Keep out of reach of children. If swallowed, get medical help or contact a Poison Control Center right away.

Directions

For Sunscreen Use:

- apply generously and evenly 15 minutes before sun exposure
- reapply at least every 2 hours
- use a water resistant sunscreen if swimming or sweating
- Sun Protection Measures. Spending time in the sun increases your risk of skin cancer and early skin aging. To decrease this risk, regularly use a sunscreen with a Broad Spectrum value of SPF of 15 or higher and other sun protection measures including:
  - limit time in the sun, especially from 10 a.m. – 2 p.m.
  - wear long-sleeved shirts, pants, hats, and sunglasses
  - children under 6 months of age: Ask a doctor

Other information

- protect this product from excessive heat and direct sun
- may stain some fabrics

Inactive ingredients

Water, Octyldodecyl Neopentanoate, Glycerin, Emulsifying Wax, Glyceryl Stearate, PEG-100 Stearate, Dimethicone, Phenoxyethanol, Ethylhexylglycerin, Caprylyl Glycol, Carbomer, Triethanolamine, Methylparaben, Disodium EDTA, Ethylene Brassylate, Dipropylene Glycol, Dimethyl Heptenal

Questions?

Visit www.neutrogena.com or call toll-free 800-582-4048 or 215-273-8755 (collect)

Distributed by:
JOHNSON & JOHNSON CONSUMER INC.
Skillman, NJ 08558

PRINCIPAL DISPLAY PANEL - 118 mL Bottle Carton

oil-free
moisture

with
sunscreen

BROAD SPECTRUM
SPF 15

facial moisturizer
with sun protection

non-comedogenic
(doesn't clog pores)

Neutrogena®

DERMATOLOGIST RECOMMENDED

4 FL. OZ. (118mL)